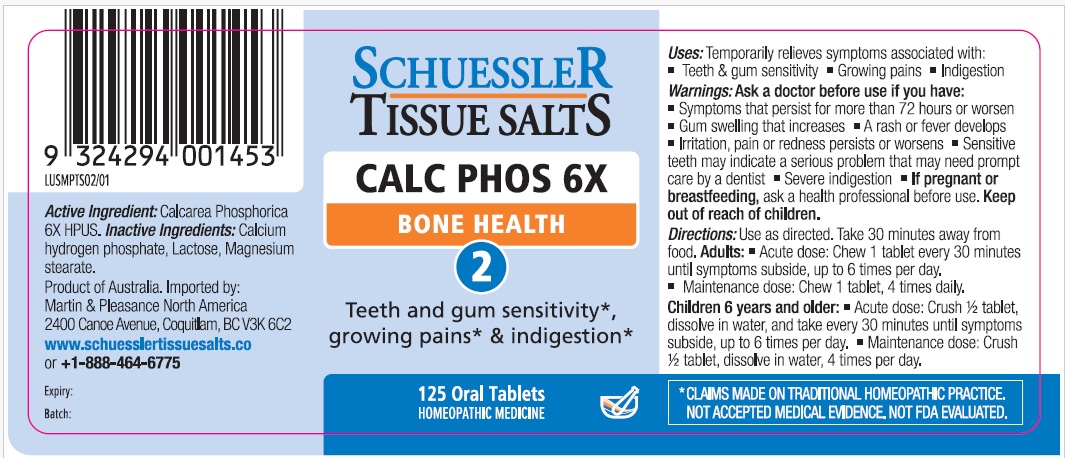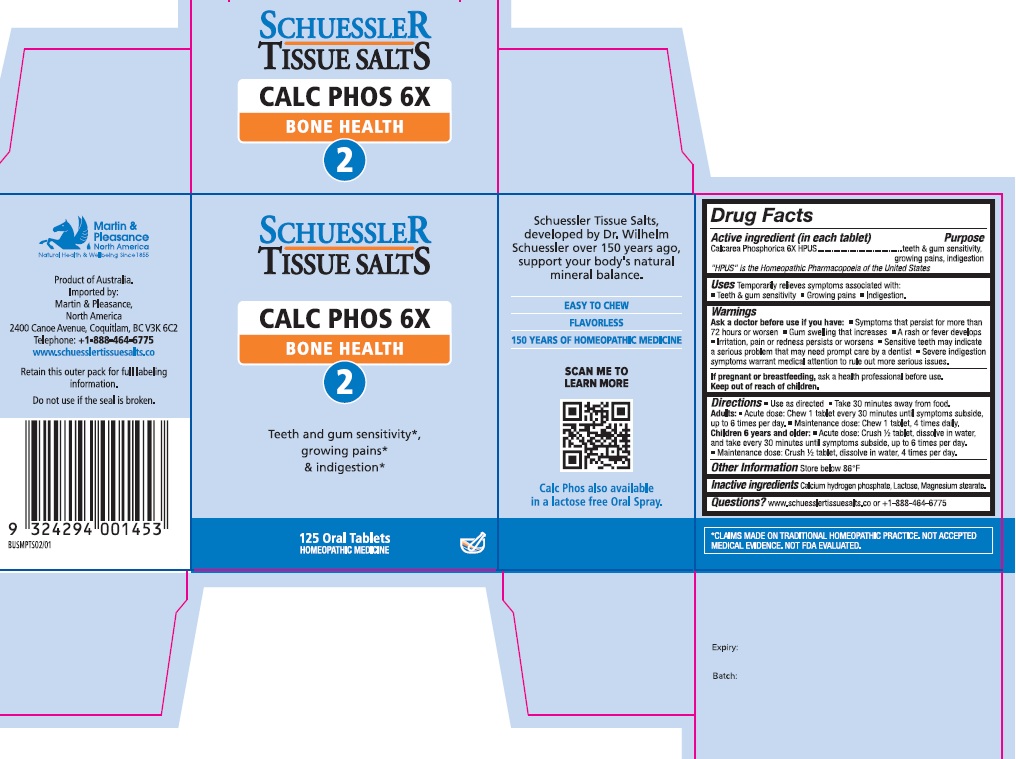 DRUG LABEL: Schuessler Tissue Salts Calc Phos Bone Health 2
NDC: 84999-014 | Form: TABLET, CHEWABLE
Manufacturer: Martin & Pleasance Pty Ltd
Category: homeopathic | Type: HUMAN OTC DRUG LABEL
Date: 20250718

ACTIVE INGREDIENTS: ANHYDROUS DIBASIC CALCIUM PHOSPHATE 6 [hp_X]/1 1
INACTIVE INGREDIENTS: LACTOSE MONOHYDRATE; MAGNESIUM STEARATE

Active Ingredients Purpose

Calcarea phosphorica 6X HPUS teeth & gum sensitivity, growing pains, indigestion

" HPUS" is the Homeopathic Pharmacopoeia of the United States

Uses

Temporarily relieves symptoms associated with

- Teeth & gum sensitivity
- Growing pains
- Indigestion

Warnings

Ask a doctor before use if you have:

- Symptoms that persist for more than 72 hours or worsen
- Gum swelling that increases
- A rash or fever develops
- Irritation, pain or redness persists or worsens
- Sensitive teeth may indicate a serious problem that may need prompt care by a dentist
- Severe indigestion symptoms warrant medical attention to rule out more serious issues.

If pregnant or breastfeeding, ask a health professional before use. Keep out of reach of children.

Directions

- Use as directed
- Take 30 minutes away from food

Adults: Acute dose: Chew 1 tablet every 30 minutes until symptoms subside up to 6 times per day.

Maintenance dose: Chew 1 tablet, 4 times daily.

Children 6 years and older: Acute dose: Crush 1/2 tablet, dissolve in water, and take every 30 minutes until symptoms subside, up to six times per day.

Maintenance dose :Crush 1/2 tablet, dissolve in water, 4 times per day.

Other Information

Store below 86°F

Inactive Ingredients

Calcium hydrogen phosphate, Lactose, Magnesium stearate

Questions?www.schuesslertissuesalts.co or + 1-888-464-6775